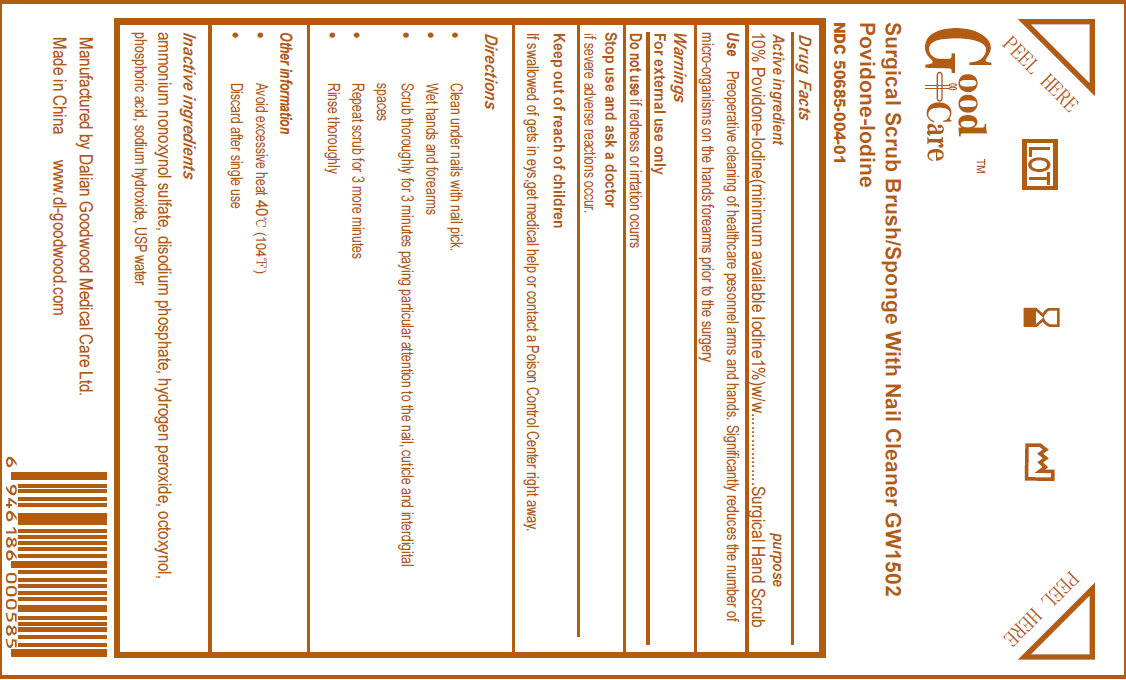 DRUG LABEL: Good Care Surgical Brush With Nail Cleaner
NDC: 50685-004 | Form: SPONGE
Manufacturer: Dalian Goodwood Medical Care Ltd.
Category: otc | Type: HUMAN OTC DRUG LABEL
Date: 20230525

ACTIVE INGREDIENTS: POVIDONE-IODINE 10 mg/1 mL
INACTIVE INGREDIENTS: AMMONIUM NONOXYNOL-4 SULFATE; SODIUM PHOSPHATE, DIBASIC, DIHYDRATE; HYDROGEN PEROXIDE; PHOSPHORIC ACID; SODIUM HYDROXIDE; WATER

Surgical Scrub Brush/Sponge With Nail Cleaner Povidone Iodine

Active Ingredient

Povidone Iodine USP, 10% w/v

(minimum available Iodine 1%) w/w

Purpose

Surgical Hand Scrub

Use

Preoperative cleaning of healthcare personnel arms and hands. Significantly reduces the number of micro-organisms on the hands forearms prior to the surgery.

Warnings

For external use only.

Do not use if redness or irritation occur

Stop use and ask a doctor if severe adverse reactions occur.

Keep out of reach of children. If swallowed or gets in eyes, get medical help or contact a Poison Control Center right away.

Directions

- Clean under nails with nail pick
- Wet hands and forearms
- Scrub thoroughly for 3 minutes paying particular attention to the nail, cuticle and interdigital spaces
- Repeat scrub for 3 more minutes
- Rinse thoroughly

Other information

- Avoid excessive heat 40 degrees C (104 degrees F)
- Discard after single use

Inactive ingredients

ammonium nonoxynol sulfate, disodium phosphate, hydrogen peroxide, octoxynol, phosphoric acid, sodium hydroxide, USP water

Manufactured by DALIAN GOODWOOD MEDICAL CARE LTD.

Made in China www.dl-goodwood.com

PACKAGE LABEL

Good Care
Surgical Scrub Brush/ Sponge With Nail Cleaner GW1503
Povidone-Iodine